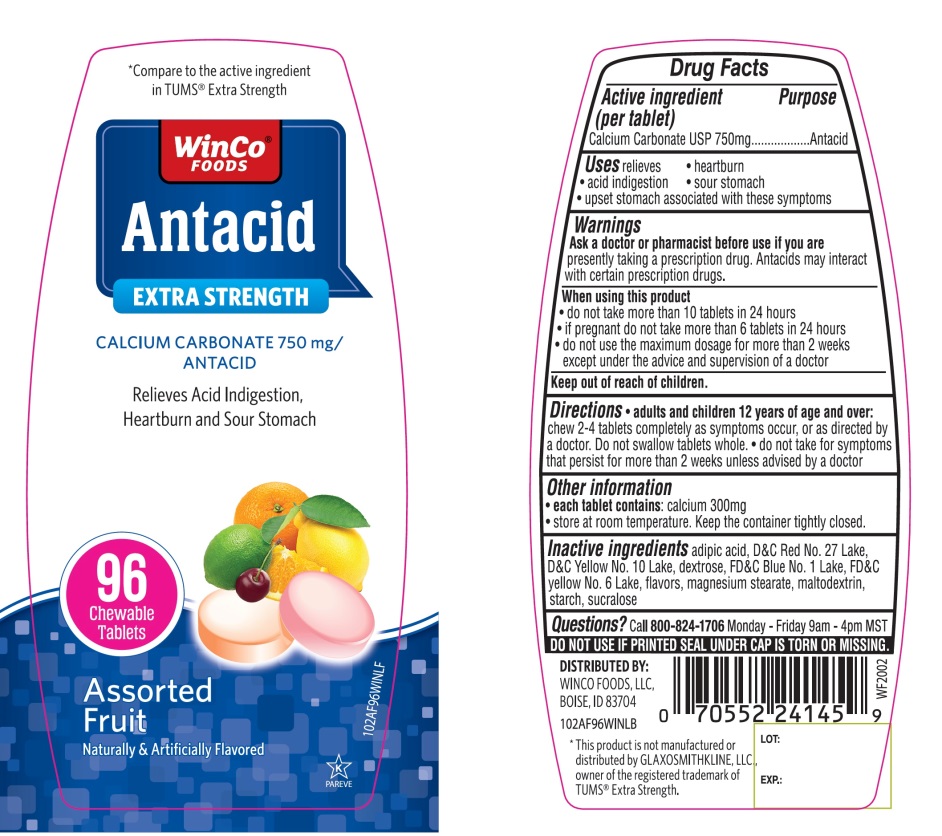 DRUG LABEL: WinCo FOODS Antacid

NDC: 67091-360 | Form: TABLET, CHEWABLE
Manufacturer: WINCO FOODS, LLC
Category: otc | Type: HUMAN OTC DRUG LABEL
Date: 20251202

ACTIVE INGREDIENTS: CALCIUM CARBONATE 750 mg/1 1
INACTIVE INGREDIENTS: ADIPIC ACID; D&C RED NO. 27; D&C YELLOW NO. 10; DEXTROSE, UNSPECIFIED FORM; FD&C BLUE NO. 1; FD&C YELLOW NO. 6; MAGNESIUM STEARATE; MALTODEXTRIN; STARCH, CORN; SUCRALOSE

WinCo®FOODS Antacid Extra Strength Assorted Fruit Tablets Drug Facts

Active ingredient (per tablet)

Calcium Carbonate USP 750mg

Purpose

Antacid

Uses

relieves

- heartburn
- sour stomach
- acid indigestion
- upset stomach associated with these symptoms

Warnings

Ask a doctor or pharmacist before use if you are

- presently taking a prescription drug. Antacids may interact with certain prescription drugs.

When using this product

- do not take more than 10 tablets in 24 hours
- if pregnant do not take more than 6 tablets in 24 hours
- do not use the maximum dosage for more than 2 weeks except under the advice and supervision of a doctor

Directions

- adults and children 12 years of age and over: chew 2 - 4 tablets completely as symptoms occur, or as directed by a doctor. Do not swallow tablets whole.
- do not take for symptoms that persist for more than 2 weeks unless advised by a doctor

Other information

- each tablet contains:calcium 300 mg
- store at room temperature. Keep the container tightly closed.

Inactive ingredients

adipic acid, D&C Red No. 27 Lake, D&C Yellow 10 Lake, dextrose, FD &C Blue No. 1 Lake, FD&C Yellow No. 6 Lake, flavors, magnesium stearate, maltodextrin, starch, sucralose.

Questions or comments?

Call 1-800-824-1706 Monday – Friday 9am – 4pm MST.

SAFETY SEALED. DO NOT USE IF PRINTED SEAL UNDER CAP IS TORN OR MISSING.

Principal Display Panel

NDC 67091-360-96

*Compare to the active ingredient in TUMS®Extra Strength

WinCo®FOODS

Antacid

EXTRA STRENGTH

CALCIUM CARBONATE 750 mg/ANTACID

Relieves Acid Indigestion, Heartburn and Sour Stomach

96 Chewable Tablets

Assorted Fruit Flavor

Naturally and Artificially Flavored

K PAREVE

GLUTEN FREE

DISTRIBUTED BY:WINCO FOODS, LLC

BOISE, ID 83704

*This product is not manufactured or distributed by GLAXOSMITHKLINE LLC, owner of the registered trademark, of TUMS®Extra Strength.